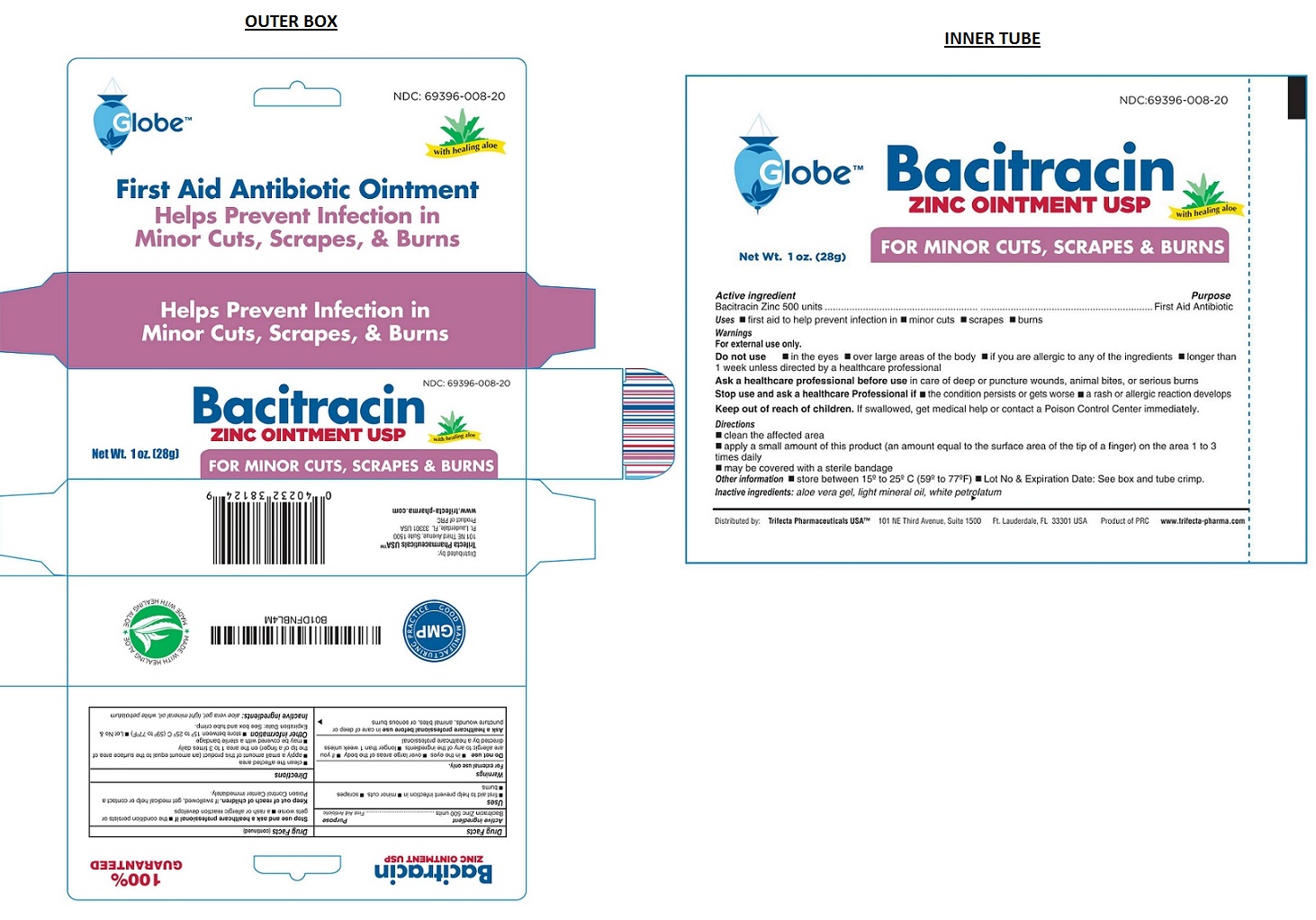 DRUG LABEL: Bacitracin Zinc
NDC: 69396-008 | Form: OINTMENT
Manufacturer: Trifecta Pharmaceuticals Usa Llc
Category: otc | Type: HUMAN OTC DRUG LABEL
Date: 20160407

ACTIVE INGREDIENTS: BACITRACIN ZINC 500 [USP'U]/1 g
INACTIVE INGREDIENTS: ALOE VERA LEAF; LIGHT MINERAL OIL; PETROLATUM

Bacitracin ZINC OINTMENT USP

Active ingredient

Bacitracin Zinc 500 units

Purpose

First Aid Antibiotic

Keep out of reach of children. If swallowed, get medical help or contact a Poison Control Center immediately.

Uses

● first aid to help prevent infection in ● minor cuts ● scrapes ● burns

Warnings

For external use only.

Do not use ● in the eyes ●over large areas of the body ● if you are allergic to any of the ingredients ● longer than 1 week unless directed by a healthcare professional

Ask a healthcare professional before use in care of deep or puncture wounds, animal bites, or serious burns

Stop use and ask a healthcare professional if ● the condition persists or gets worse ● a rash or allergic reaction develops

Directions

● clean the affected area
● apply a small amount of this product (an amount equal to the surface area of the tip of a finger) on the area 1 to 3 times daily
● may be covered with a sterile bandage

Inactive ingredient:

aloe vera gel, light mineral oil, white petrolatum

Other information

● store between15° to 25°C (59° to 77°F) ● Lot No & Expiration Date: See box and tube crimp.

100% GUARANTEED

Distributed by:

Trifecta Pharmaceuticals USA™

101 NE Third Avenue, Suite 1500

Ft. Lauderdale, FL 33301 USA

Product of PRC

www.trifecta-pharma.com